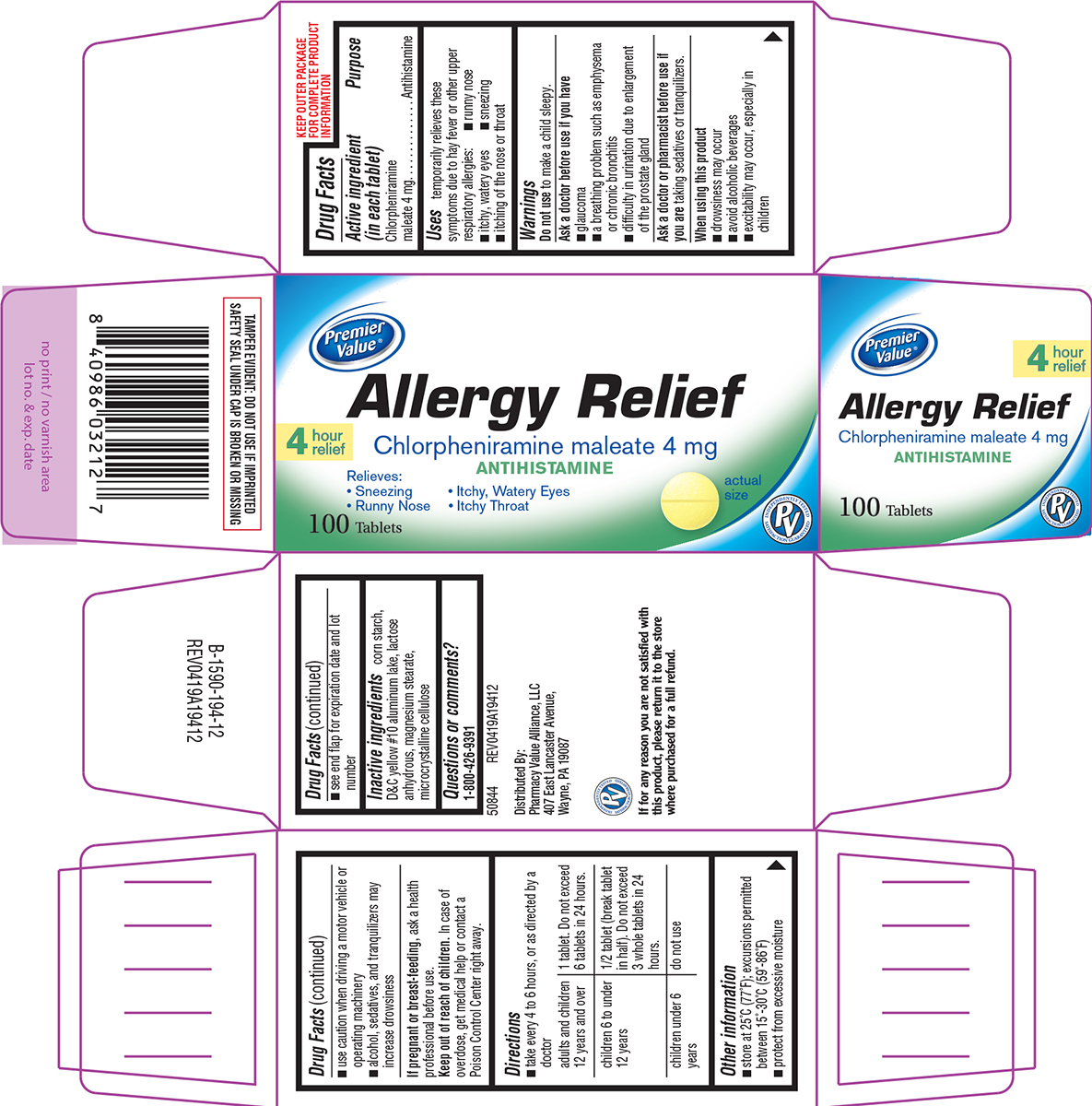 DRUG LABEL: Allergy Relief
NDC: 68016-683 | Form: TABLET
Manufacturer: Chain Drug Consortium
Category: otc | Type: HUMAN OTC DRUG LABEL
Date: 20250719

ACTIVE INGREDIENTS: CHLORPHENIRAMINE MALEATE 4 mg/1 1
INACTIVE INGREDIENTS: STARCH, CORN; D&C YELLOW NO. 10 ALUMINUM LAKE; ANHYDROUS LACTOSE; MAGNESIUM STEARATE; MICROCRYSTALLINE CELLULOSE

Premier Value 44-194 Delisted

Active ingredient (in each tablet)

Chlorpheniramine maleate 4 mg

Purpose

Antihistamine

Uses

temporarily relieves these symptoms due to hay fever or other upper respiratory allergies:

- runny nose
- itchy, watery eyes
- sneezing
- itching of the nose or throat

Warnings

Do not use

to make a child sleepy.

Ask a doctor before use if you have

- glaucoma
- a breathing problem such as emphysema or chronic bronchitis
- difficulty in urination due to enlargement of the prostate gland

Ask a doctor or pharmacist before use if you are

taking sedatives or tranquilizers.

When using this product

- drowsiness may occur
- avoid alcoholic beverages
- alcohol, sedatives, and tranquilizers may increase drowsiness
- use caution when driving a motor vehicle or operating machinery
- excitability may occur, especially in children

If pregnant or breast-feeding,

ask a health professional before use.

Keep out of reach of children.

In case of overdose, get medical help or contact a Poison Control Center right away.

Directions

- take every 4 to 6 hours, or as directed by a doctor

adults and children 12 years and over | 1 tablet. Do not exceed 6 tablets in 24 hours.
children 6 to under 12 years | 1/2 tablet (break tablet in half). Do not exceed 3 whole tablets in 24 hours.
children under 6 years | do not use

Other information

- protect from excessive moisture
- store at 25°C (77°F); excursions permitted between 15°-30°C (59°-86°F)
- see end flap for expiration date and lot number

Inactive ingredients

corn starch, D&C yellow #10 aluminum lake, lactose anhydrous, magnesium stearate, microcrystalline cellulose

Questions or comments?

1-800-426-9391

Principal Display Panel

Premier
Value®

4 hour
relief

Allergy Relief
Chlorpheniramine maleate 4 mg
ANTIHISTAMINE

Relieves:
• Sneezing • Itchy, Watery Eyes
• Runny Nose • Itchy Throat

100 Tablets

actual
size

PV
INDEPENDENTLY TESTED
SATISFACTION GUARANTEED

TAMPER EVIDENT: DO NOT USE IF IMPRINTED
SAFETY SEAL UNDER CAP IS BROKEN OR MISSING

50844 REV0419A19412

Distributed By:
Pharmacy Value Alliance, LLC
407 East Lancaster Avenue,
Wayne, PA 19087

If for any reason you are not satisfied with
this product, please return it to the store
where purchased for a full refund.

Premier Value 44-194